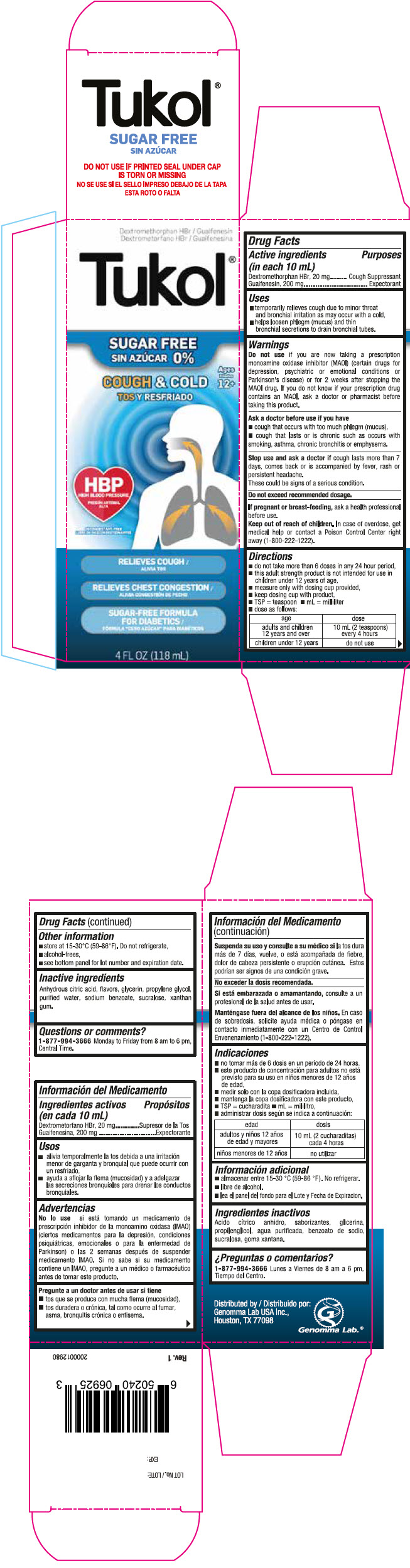 DRUG LABEL: Tukol Sugar Free Cough and Cold
NDC: 50066-505 | Form: SYRUP
Manufacturer: Genomma Lab USA
Category: otc | Type: HUMAN OTC DRUG LABEL
Date: 20241008

ACTIVE INGREDIENTS: DEXTROMETHORPHAN HYDROBROMIDE 2 mg/1 mL; GUAIFENESIN 20 mg/1 mL
INACTIVE INGREDIENTS: ANHYDROUS CITRIC ACID; GLYCERIN; PROPYLENE GLYCOL; WATER; SODIUM BENZOATE; SUCRALOSE; XANTHAN GUM

Tukol®Sugar Free Cough & Cold

Drug Facts

ACTIVE INGREDIENT

PURPOSE

Active ingredients (in each 10 mL) | Purposes
Dextromethorphan HBr, 20 mg | Cough Suppressant
Guaifenesin, 200 mg | Expectorant

Uses

- temporarily relieves cough due to minor throat and bronchial irritation as may occur with a cold,
- helps loosen phlegm (mucus) and thin bronchial secretions to drain bronchial tubes.

Warnings

DO NOT USE

Do not useif you are now taking a prescription monoamine oxidase inhibitor (MAOI) (certain drugs for depression, psychiatric or emotional conditions or Parkinson's disease) or for 2 weeks after stopping the MAOI drug. If you do not know if your prescription drug contains an MAOI, ask a doctor or pharmacist before taking this product.

Ask a doctor before use if you have

- cough that occurs with too much phlegm (mucus),
- cough that lasts or is chronic such as occurs with smoking, asthma, chronic bronchitis or emphysema.

Stop use and ask a doctor ifcough lasts more than 7 days, comes back or is accompanied by fever, rash or persistent headache.

These could be signs of a serious condition.

Do not exceed recommended dosage.

PREGNANCY OR BREAST FEEDING

If pregnant or breast-feeding,ask a health professional before use.

Keep out of reach of children.In case of overdose, get medical help or contact a Poison Control Center right away (1-800-222-1222).

Directions

- do not take more than 6 doses in any 24 hour period,
- this adult strength product is not intended for use in children under 12 years of age,
- measure only with dosing cup provided,
- keep dosing cup with product,
- TSP = teaspoon
- mL = milliliter
- dose as follows:

age | dose
adults and children 12 years and over | 10 mL (2 teaspoons) every 4 hours
children under 12 years | do not use

Other information

- store at 15-30°C (59-86°F). Do not refrigerate,
- alcohol-frees,
- see bottom panel for lot number and expiration date.

Inactive ingredients

Anhydrous citric acid, flavors, glycerin, propylene glycol, purified water, sodium benzoate, sucralose, xanthan gum.

Questions or comments?

1-877-994-3666Monday to Friday from 8 am to 6 pm, Central Time.

Distributed by:
Genomma Lab USA Inc.,
Houston, TX 77098

PRINCIPAL DISPLAY PANEL - 118 mL Bottle Carton

Dextromethorphan HBr / Guaifenesin

Tukol®

SUGAR FREE
0%

COUGH & COLD

Ages
12+

HBP
HIGH BLOOD PRESSURE

RELIEVES COUGH

RELIEVES CHEST CONGESTION

SUGAR-FREE FORMULA
FOR DIABETICS

4 FL OZ (118 mL)